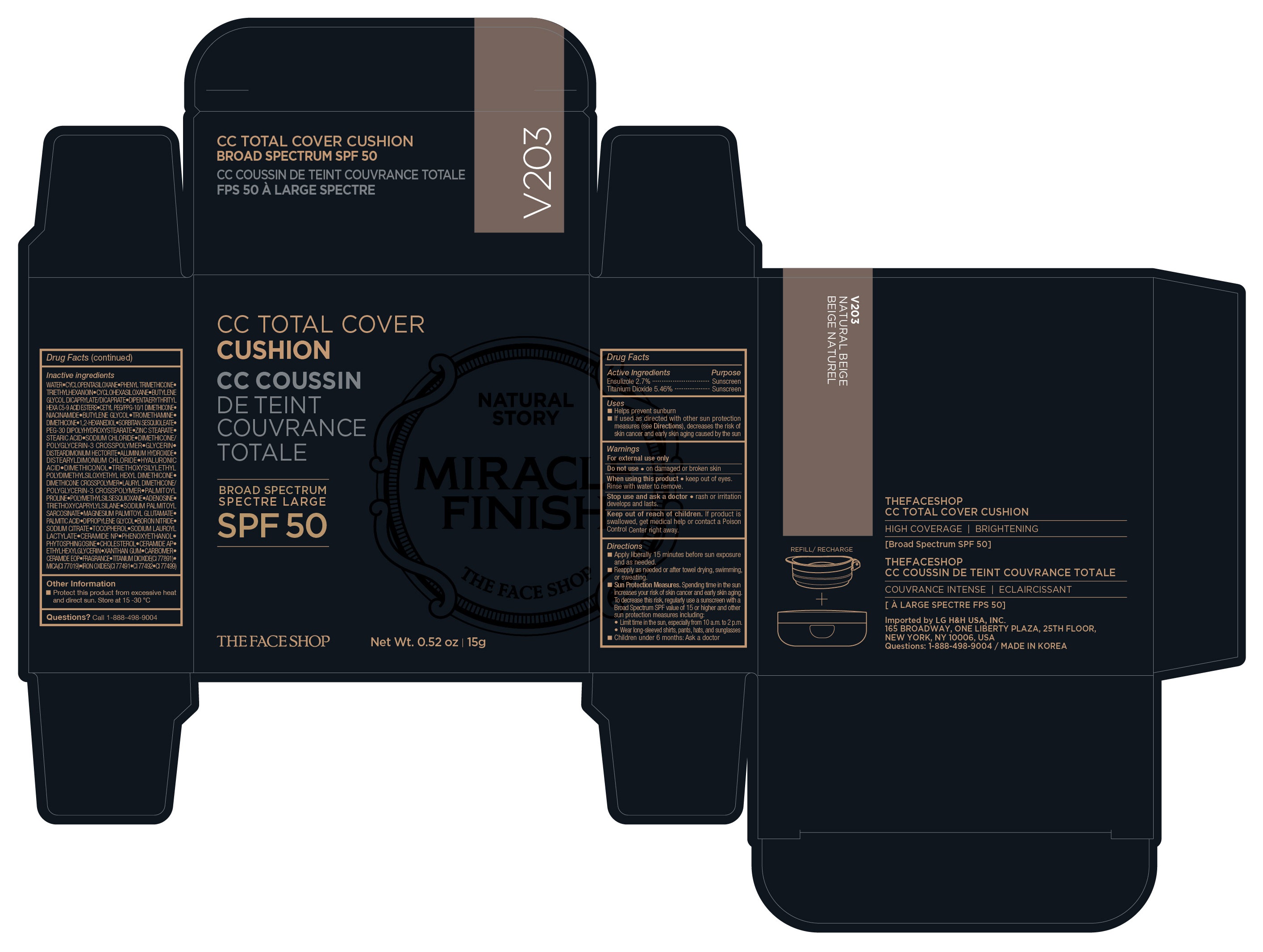 DRUG LABEL: THEFACESHOP Cushion CC Total Cover SPF 50 Natural Beige
NDC: 53208-063 | Form: POWDER
Manufacturer: LG H&H Co., Ltd.
Category: otc | Type: HUMAN OTC DRUG LABEL
Date: 20250101

ACTIVE INGREDIENTS: TITANIUM DIOXIDE 0.819 g/15 g; ENSULIZOLE 0.405 g/15 g
INACTIVE INGREDIENTS: BIOSACCHARIDE GUM-1; SILICON DIOXIDE; MICA; TRIETHOXYCAPRYLYLSILANE; SODIUM PALMITOYL SARCOSINATE; PALMITIC ACID; CALCIUM CARBONATE; ALBIZIA JULIBRISSIN BARK; BUTYLENE GLYCOL; DIMETHICONE CROSSPOLYMER (450000 MPA.S AT 12% IN CYCLOPENTASILOXANE); METHYL METHACRYLATE; DIMETHICONE/VINYL DIMETHICONE CROSSPOLYMER (HARD PARTICLE); ZINC STEARATE; DISTEARDIMONIUM HECTORITE; SODIUM CHLORIDE; SORBITAN SESQUIOLEATE; ALUMINUM HYDROXIDE; DISTEARYLDIMONIUM CHLORIDE; TRIETHYLHEXANOIN; PEG-10 DIMETHICONE (600 CST); DIPROPYLENE GLYCOL; NIACINAMIDE; TROMETHAMINE; 1,2-HEXANEDIOL; STEARIC ACID; SORBITAN SESQUIISOSTEARATE; .ALPHA.-TOCOPHEROL ACETATE; PALMITOYL PROLINE; TANGERINE PEEL; ADENOSINE; MAGNESIUM PALMITOYL GLUTAMATE; PHENOXYETHANOL; WATER

53208-063-03 THEFACESHOP CC Total Cover Cushion SPF 50 Natural Beige V203

ACTIVE INGREDIENTS

Ensulizole 2.7%

Titanium Dioxide 5.46%

PURPOSE

SUNSCREEN

USES

- Helps prevent sunbrun
- If used as directed with other sun protection measures (see Directions), decreases the risk of skin cancer and early skin aging caused by the sun

WARNINGS

For external use only

Do not useon damaged or broken skin

WHEN USING

When using this productkeep out of eyes. Rinse with water to remove.

Stop use and ask doctorrash or irritation develops and lasts.

Keep out of reach of children.If product is swallowed, get medical help or contact a Poison Control Center right away.

DIRECTIONS

- Apply liberally 15 minutes before sun exposure and as needed.
- Reapply as needed or after towel drying, swimming, or sweating.
- Sun Protection Measures.Spending time in the sun increases your risk of skin cancer and early skin aging. To decrease this risk, regularly use a sunscreen with a Broad Spectrum SPF value of 15 or higher and other sun protection measures including:

- Limit time in the sun, especially from 10 a.m. to 2 p.m.

- Wear long-sleeved shirts, pants, hats, and sunglasses

- Children under 6 months: Ask a doctor

INACTIVE INGREDIENTS

CYCLOPENTASILOXANE, WATER, TRIETHYLHEXANOIN, PEG-10 DIMETHICONE, POLYMETHYL METHACRYLATE, NIACINAMIDE, DIPROPYLENE GLYCOL, TROMETHAMINE, 1,2-HEXANEDIOL, DIMETHICONE/VINYL DIMETHICONE CROSSPOLYMER, ZINC STEARATE, DISTEARDIMONIUM HECTORITE, SODIUM CHLORIDE, STEARIC ACID, SORBITAN SESQUIISOSTEARATE, SORBITAN SESQUIOLEATE, ALUMINUM HYDROXIDE, DISTEARYLDIMONIUM CHLORIDE, TOCOPHERYL ACETATE, PALMITOYL PROLINE, CITRUS UNSHIU PEEL EXTRACT, BUTYLENE GLYCOL, ADENOSINE, TRIETHOXYCAPRYLYLSILANE, MAGNESIUM PALMITOYL GLUTAMATE, SODIUM PALMITOYL SARCOSINATE, TRIETHOXYSILYLETHYL POLYDIMETHYLSILOXYETHYL HEXYL DIMETHICONE, PHENOXYETHANOL, PALMITIC ACID, BIOSACCHARIDE GUM-1, CALCIUM CARBONATE, SILICA, ALBIZIA JULIBRISSIN BARK EXTRACT, FRAGRANCE, TITANIUM DIOXIDE(CI 77891), MICA(CI 77019), IRON OXIDES(CI 77491, CI 77492, CI 77499)

OTHER INFORMATION

- Protect this product from excessive heat and direct sun. Store at 15 - 30 °C

QUESTIONS?

Call 1-888-498-9004

PRINCIPAL DISPLAY PANEL

CC TOTAL COVER
CUSHION
BROAD SPECTRUM
SPF 50
THEFACESHOP
Net Wt. 0.52 oz | 15g

V203 NATURAL BEIGE

THEFACESHOP
CC TOTAL COVER CUSHION

HIGH COVERAGE | BRIGHTENING
[Broad Spectrum SPF 50]

Imported by LG H&H USA, INC.
165 BROADWAY, ONE LIBERTY PLAZA, 25TH FLOOR
NEW YORK, NY 10006, USA

Questions: 1-888-498-9004 / MADE IN KOREA